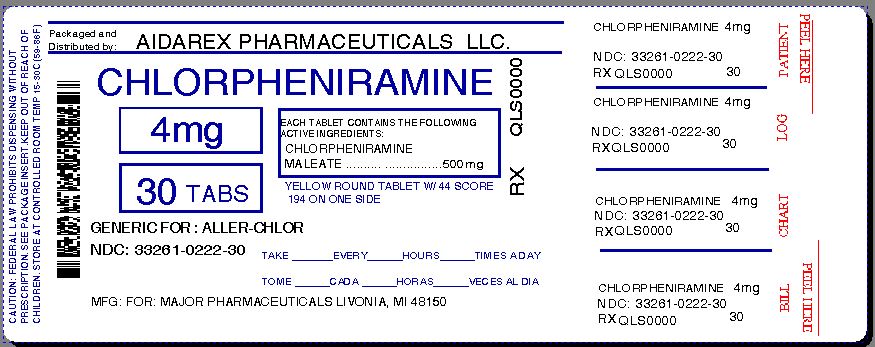 DRUG LABEL: Allergy
NDC: 33261-222 | Form: TABLET
Manufacturer: Aidarex Pharmaceuticals LLC
Category: otc | Type: HUMAN OTC DRUG LABEL
Date: 20131216

ACTIVE INGREDIENTS: CHLORPHENIRAMINE MALEATE 4 mg/1 1
INACTIVE INGREDIENTS: ANHYDROUS LACTOSE; D&C YELLOW NO. 10; MAGNESIUM STEARATE; CELLULOSE, MICROCRYSTALLINE

Major 44-194

Active ingredient (in each tablet)

Chlorpheniramine maleate 4 mg

Purpose

Antihistamine

Use

- temporarily relieves these symptoms due to hay fever or other upper respiratory allergies:
  - runny nose
  - itchy, watery eyes
  - sneezing
  - itching of the nose or throat

Warnings

Ask a doctor before use if you have

- glaucoma
- a breathing problem such as emphysema or chronic bronchitis
- trouble urinating due to an enlarged prostate gland

Ask a doctor or pharmacist before use if you are

taking sedatives or tranquilizers.

When using this product

- drowsiness may occur
- avoid alcoholic beverages
- alcohol, sedatives, and tranquilizers may increase drowsiness
- use caution when driving a motor vehicle or operating machinery
- excitability may occur, especially in children

If pregnant or breast-feeding,

ask a health professional before use.

Keep out of reach of children.

In case of overdose, get medical help or contact a Poison Control Center right away.

Directions

adults and children 12 years of age and older | 1 tablet every 4 to 6 hours. Do not take more than 6 tablets in 24 hours
children 6 to under 12 years of age | 1/2 tablet (break tablet in half) every 4 to 6 hours. Do not exceed 3 tablets in 24 hours.
children under 6 years of age | do not use this product in children under 6 years of age

Other information

- store at 25ºC (77ºF); excursions permitted between 15º-30ºC (59º-86ºF)
- protect from excessive moisture
- see end flap for expiration date and lot number

Inactive ingredients

corn starch, D&C yellow #10 aluminum lake, lactose anhydrous, magnesium stearate, microcrystalline cellulose

Questions or comments?

(800) 616-2471

Principal Display Panel

NDC 33261-0222-30

Allergy
Tablets
Antihistamine

RELIEVES: Sneezing,
Itchy, Watery Eyes,
Itchy Throat, Runny Nose

*Compare to the active ingredient in Chlor-Trimeton® Allergy Tablets

Chlorpheniramine maleate 4 mg EACH

4 hour
24 TABLETS

*This product is not manufactured or distributed by McNeil Consumer Healthcare, owner of the registered trademark Chlor-Trimeton® Allergy Tablets.
50844 REV0512K19408

Distributed by Major Pharmaceuticals
31778 Enterprise Drive
Livonia, MI 48150 USA

Repackaged By :
Aidarex Pharmaceuticals LLC,
Corona, CA 92880

REV. 05/12
M-17

TAMPER EVIDENT: DO NOT USE IF CARTON IS OPENED OR IF BLISTER UNIT IS TORN, BROKEN OR SHOWS ANY SIGNS OF TAMPERING.